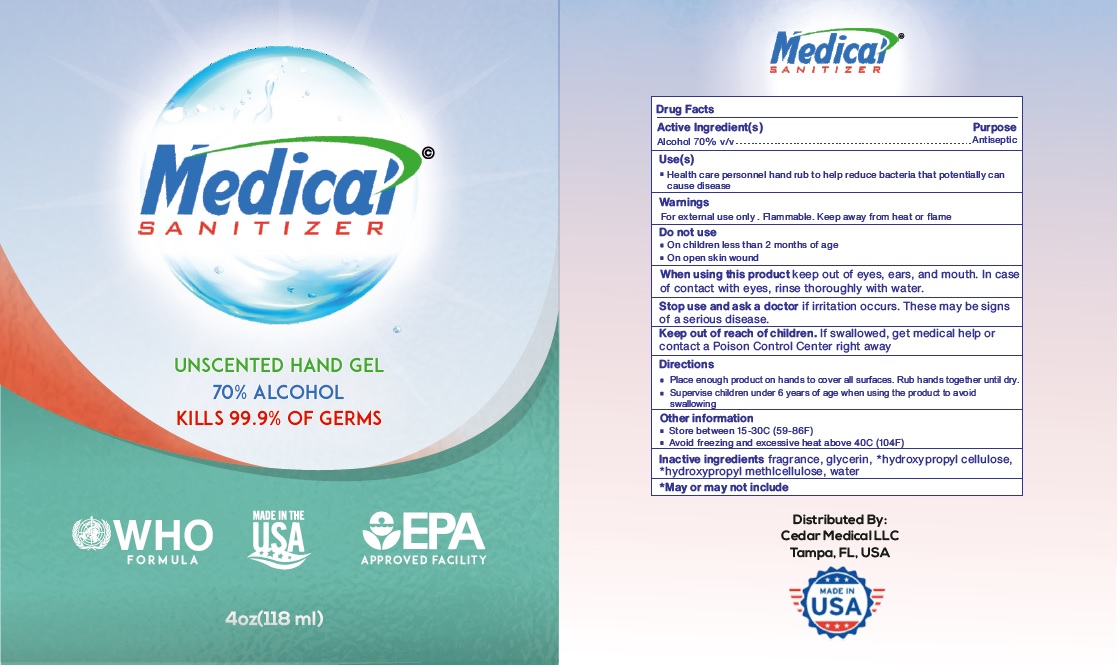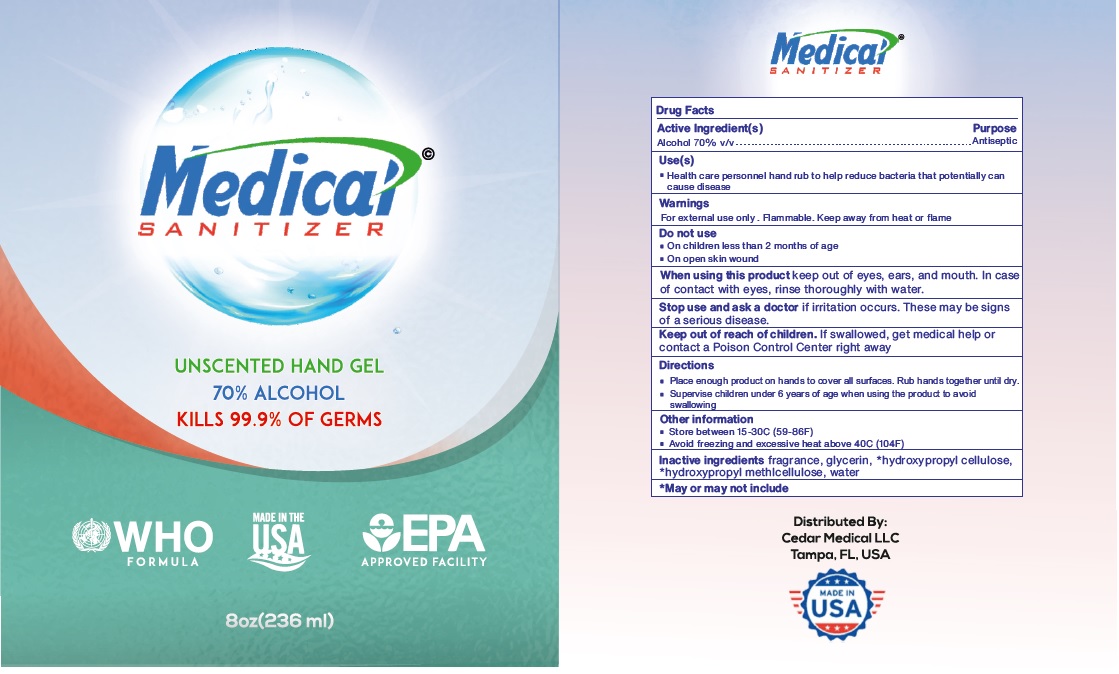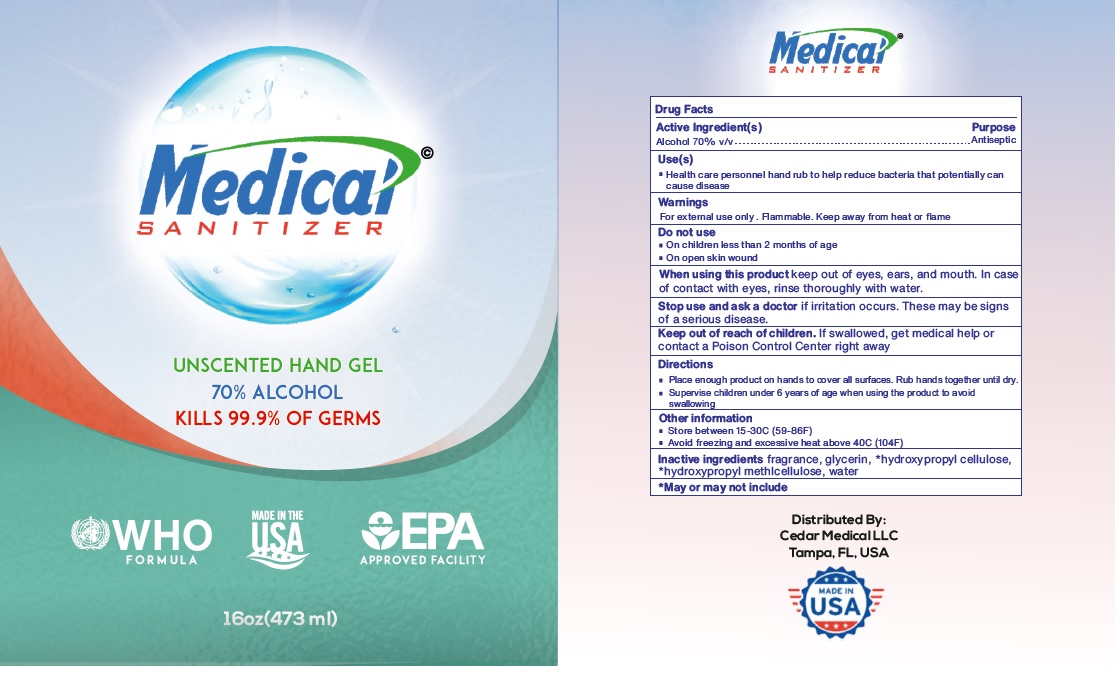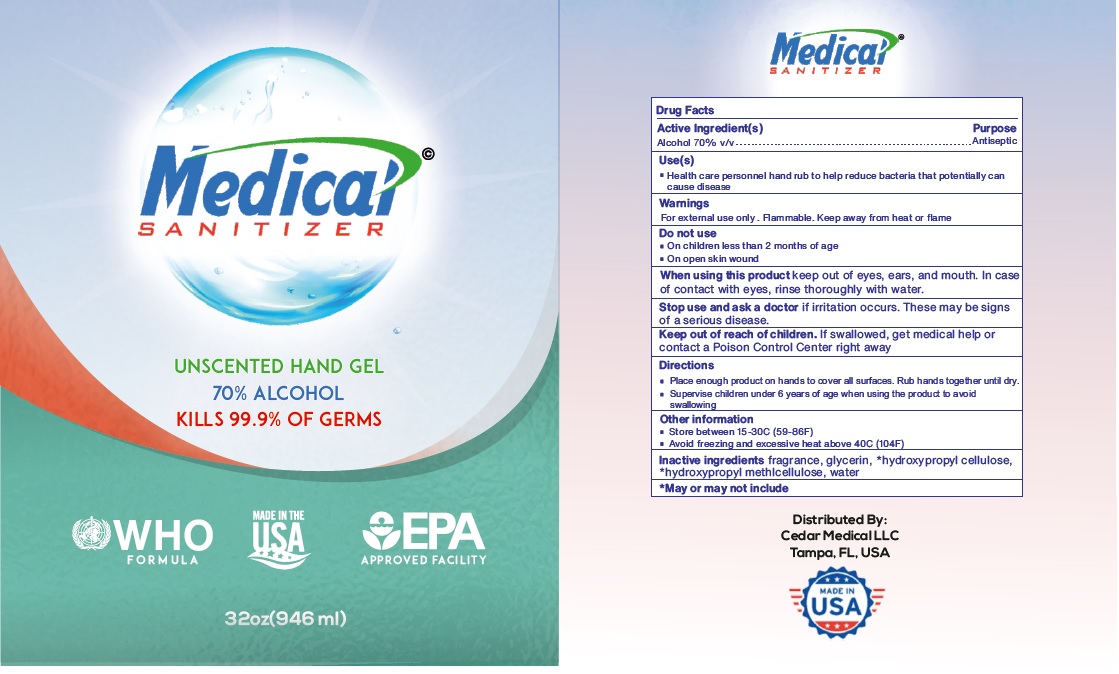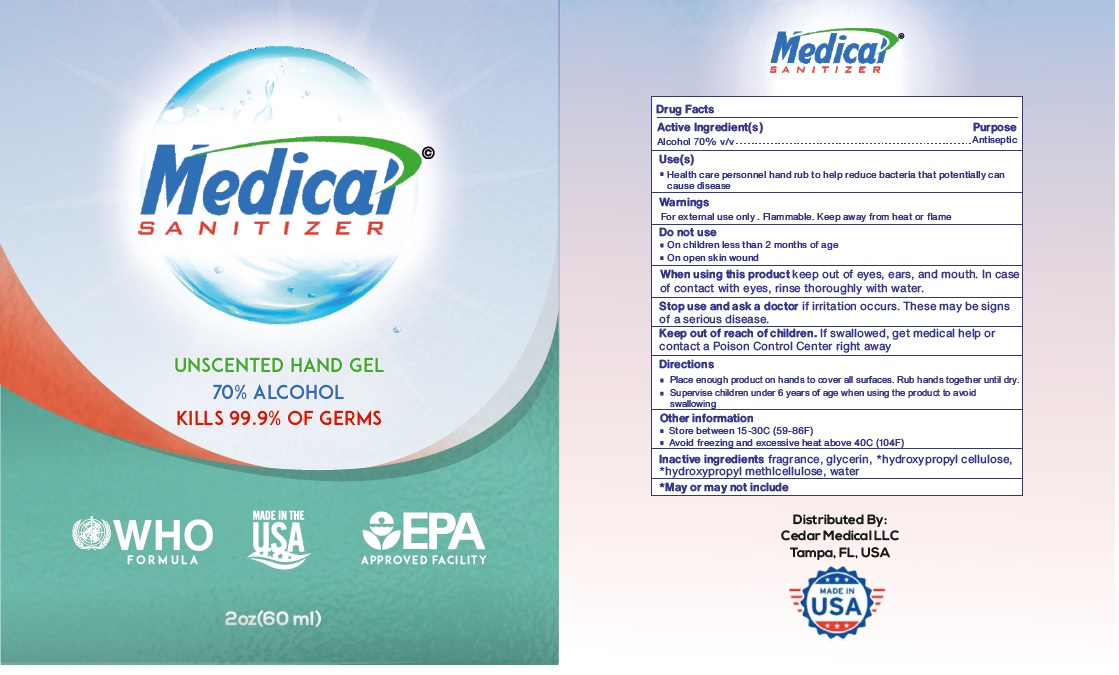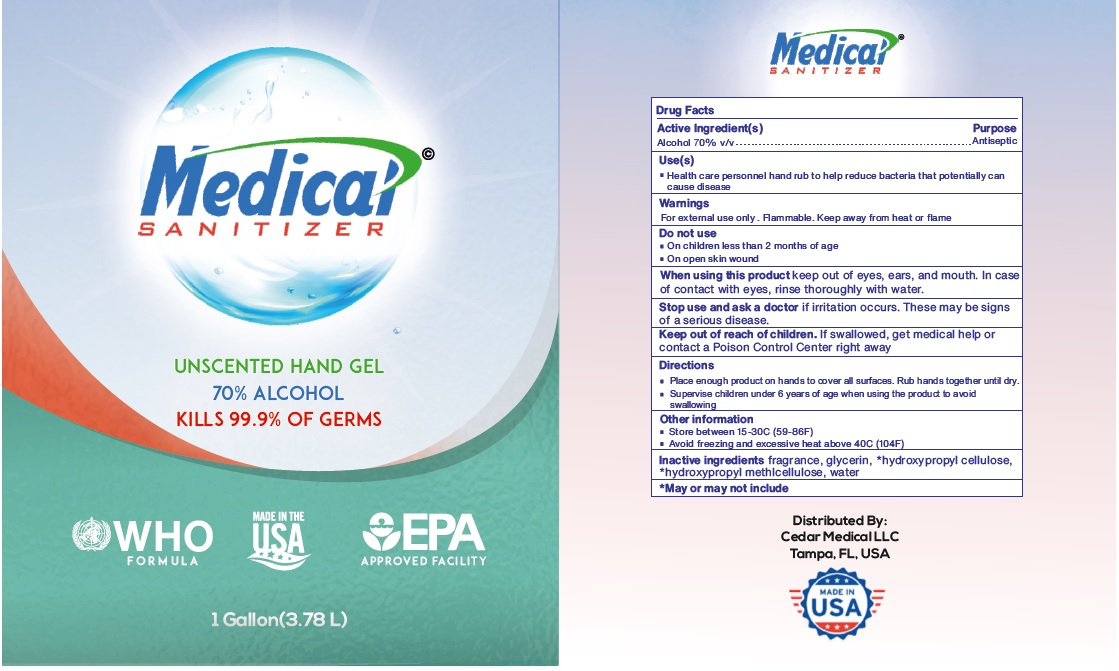 DRUG LABEL: Medical Sanitizer
NDC: 80101-102 | Form: GEL
Manufacturer: Cedar Medical Llc
Category: otc | Type: HUMAN OTC DRUG LABEL
Date: 20200818

ACTIVE INGREDIENTS: ALCOHOL 70 mL/100 mL
INACTIVE INGREDIENTS: GLYCERIN; HYDROXYPROPYL CELLULOSE, UNSPECIFIED; HYPROMELLOSE, UNSPECIFIED; WATER

Medical© SANITIZER

Active Ingredient(s)

Alcohol 70% v/v

Purpose

Antiseptic

Use(s)

• Health care personnel hand rub to help reduce bacteria that potentially can cause disease

Warnings

For external use only. Flammable. Keep away from heat or flame

Do not use

• On children less than 2 months of age

• On open skin wound

When using this product keep out of eyes, ears, and mouth. In case of contact with eyes, rinse thoroughly with water.

Stop use and ask a doctor if irritation occurs. These may be signs of a serious disease.

Keep out of reach of children. If swallowed, get medical help or contact a Poison Control Center right away

Directions

• Place enough product on hands to cover all surfaces. Rub hands together until dry.

• Supervise children under 6 years of age when using the product to avoid swallowing

Other information

• Store between 15-30C (59-86F)

• Avoid freezing and excessive heat above 40C (104F)

INACTIVE INGREDIENT

Inactive ingredients fragrance, glycerin, *hydroxypropyl cellulose, *hydroxypropyl methylcellulose, water

*May or may not include

UNSCENTED HAND GEL

KILLS 99.9% OF GERMS

WHO FORMULA

MADE IN THE USA

EPA APPROVED FACILITY

Distributed By:

Cedar Medical LLC

Tampa, FL, USA